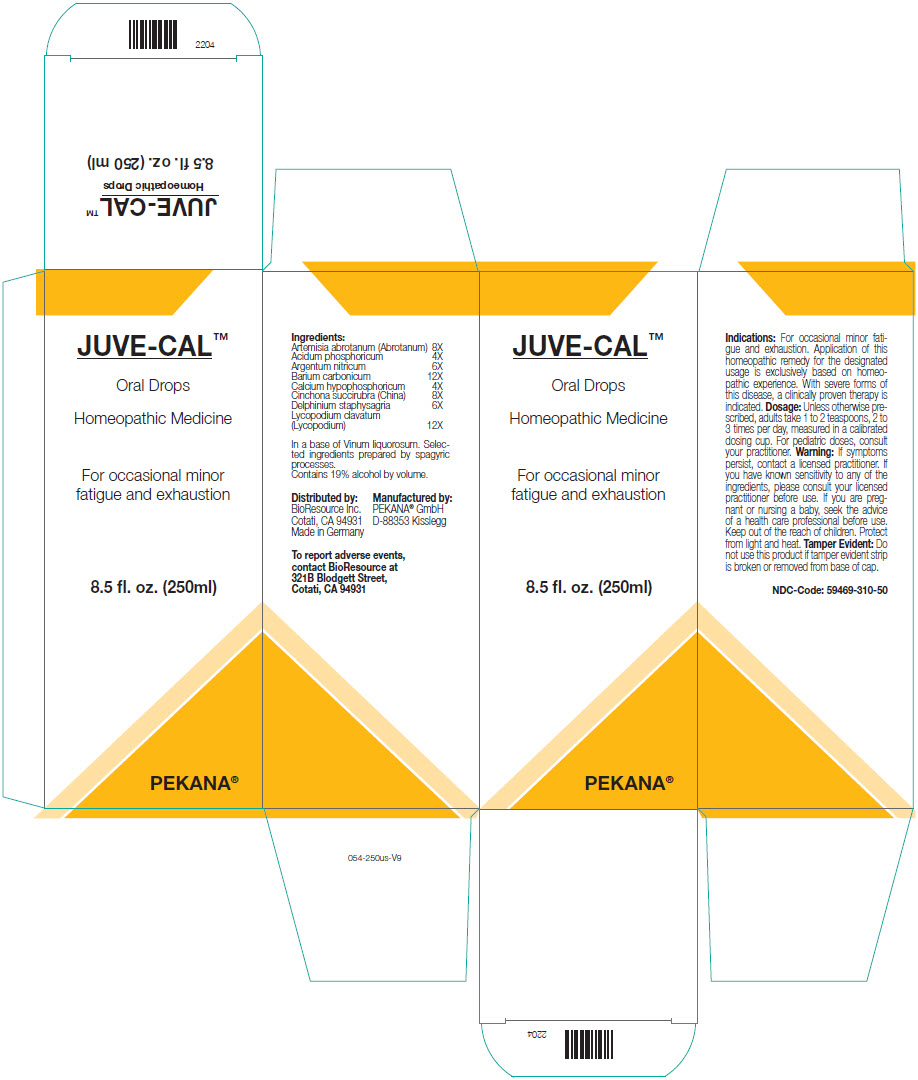 DRUG LABEL: JUVE-CAL
NDC: 59469-310 | Form: SYRUP
Manufacturer: PEKANA Naturheilmittel GmbH
Category: homeopathic | Type: HUMAN OTC DRUG LABEL
Date: 20230111

ACTIVE INGREDIENTS: ARTEMISIA ABROTANUM FLOWERING TOP 8 [hp_X]/250 mL; PHOSPHORIC ACID 4 [hp_X]/250 mL; SILVER NITRATE 6 [hp_X]/250 mL; BARIUM CARBONATE 12 [hp_X]/250 mL; LYCOPODIUM CLAVATUM SPORE 12 [hp_X]/250 mL; DELPHINIUM STAPHISAGRIA SEED 6 [hp_X]/250 mL; CALCIUM HYPOPHOSPHITE 4 [hp_X]/250 mL; CINCHONA OFFICINALIS BARK 8 [hp_X]/250 mL
INACTIVE INGREDIENTS: WATER; ALCOHOL

JUVE-CAL™

ACTIVE INGREDIENT

Ingredients:
Artemisia abrotanum (Abrotanum) | 8X
Acidum phosphoricum | 4X
Argentum nitricum | 6X
Barium carbonicum | 12X
Calcium hypophosphoricum | 4X
Cinchona succirubra (China) | 8X
Delphinium staphysagria | 6X
Lycopodium clavatum (Lycopodium) | 12X

INACTIVE INGREDIENT

In a base of Vinum liquorosum. Selected ingredients prepared by spagyric processes.

Contains 19% alcohol by volume.

Indications

PURPOSE

For occasional minor fatigue and exhaustion. Application of this homeopathic remedy for the designated usage is exclusively based on homeopathic experience. With severe forms of this disease, a clinically proven therapy is indicated.

Dosage

Unless otherwise prescribed, adults take 1 to 2 teaspoons, 2 to 3 times per day, measured in a calibrated dosing cup. For pediatric doses, consult your practitioner.

Warning

ASK DOCTOR

If symptoms persist, contact a licensed practitioner. If you have known sensitivity to any of the ingredients, please consult your licensed practitioner before use. If you are pregnant or nursing a baby, seek the advice of a health care professional before use.

Keep out of the reach of children.

STORAGE AND HANDLING

Protect from light and heat.

Tamper Evident

Do not use this product if tamper evident strip is broken or removed from base of cap.

QUESTIONS

To report adverse events, contact BioResource at 321B Blodgett Street, Cotati, CA 94931

Distributed by:
BioResource Inc.
Cotati, CA 94931

Manufactured by:
PEKANA® GmbH
D-88353 Kisslegg

PRINCIPAL DISPLAY PANEL - 250 ml Bottle Box

JUVE-CAL™

Oral Drops

Homeopathic Medicine

For occasional minor
fatigue and exhaustion

8.5 fl. oz. (250ml)

PEKANA®